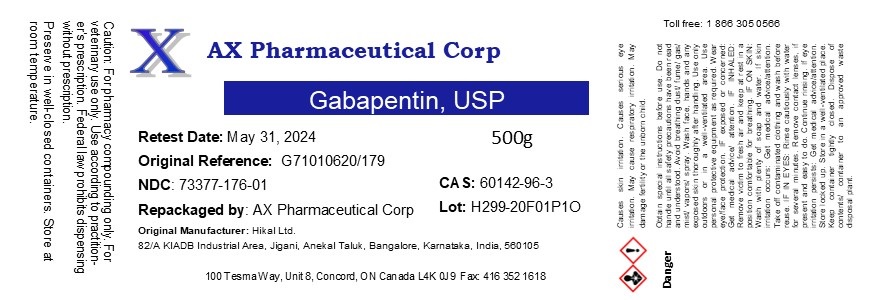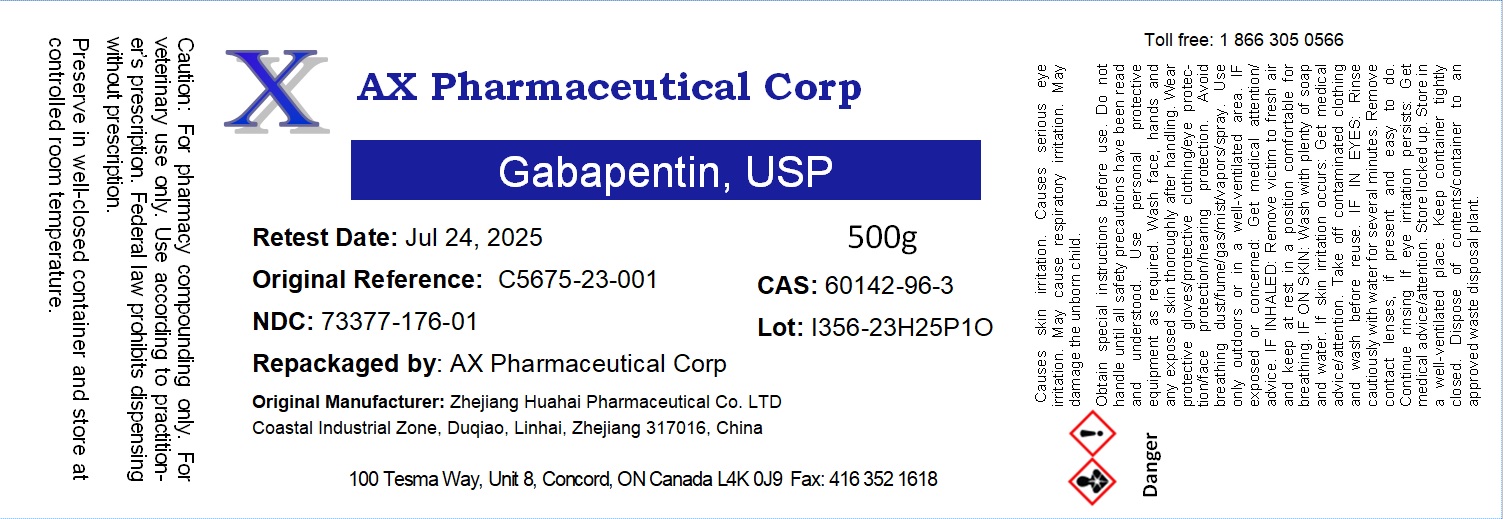 DRUG LABEL: Gabapentin
NDC: 73377-176 | Form: POWDER
Manufacturer: AX Pharmaceutical Corp
Category: other | Type: BULK INGREDIENT - ANIMAL DRUG
Date: 20240215

ACTIVE INGREDIENTS: GABAPENTIN 1 g/1 g

Gabapentin